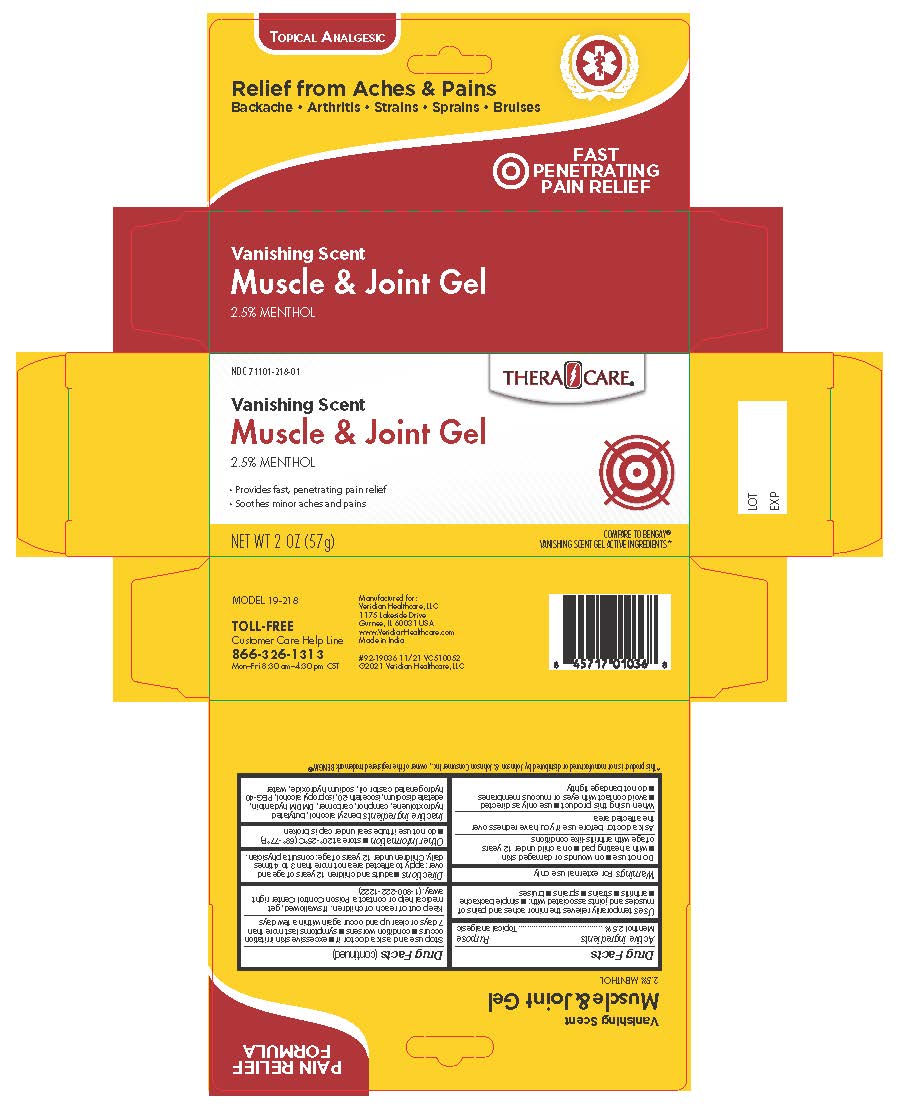 DRUG LABEL: TheraCare Pain Relieving Muscle Vanishing Scent
NDC: 71101-218 | Form: GEL
Manufacturer: Veridian Healthcare
Category: otc | Type: HUMAN OTC DRUG LABEL
Date: 20251227

ACTIVE INGREDIENTS: MENTHOL, UNSPECIFIED FORM 25 mg/1 g
INACTIVE INGREDIENTS: BUTYLATED HYDROXYTOLUENE; EDETATE DISODIUM; BENZYL ALCOHOL; CAMPHOR (NATURAL); CARBOMER 940; DMDM HYDANTOIN; ISOCETETH-20; ISOPROPYL ALCOHOL; POLYOXYL 40 HYDROGENATED CASTOR OIL; SODIUM HYDROXIDE; WATER

TheraCare Pain Relieving Muscle Vanishing Scent Rub

Drug Facts

Active ingredient

Menthol 2.5%

Purpose

Topical analgesic

Uses

temporarily relieves the minor aches and pains of muscles and joints associated with:

- simple backache
- arthritis
- strains
- bruises
- sprains

Warnings

For external use only.

Do not use

- on wounds or damaged skin
- with a heating pad
- on a child under 12 years of age with arthritis-like conditions

Ask a doctor before use if you have redness over the affected area

When using this product

- use only as directed
- avoid contact with eyes or mucous membranes
- do not bandage tightly

Stop use and ask a doctor if

- excessive skin irritation occurs
- condition worsens
- symptoms last more than 7 days or clear up and occur again within a few days

Keep out of reach of children. If swallowed, get medical help or contact a Poison Control Center right away. (1-800-222-1222)

Directions

- adults and children 12 years of age and over: apply to affected area not more than 3 to 4 times daily
- children under 12 years of age: consult physician

Other information

store at 20° to 25°C (68° to 77°F)

- Do not use if tube seal under cap is broken

Inactive ingredients

benzyl alcohol, butylated hydroxtoluene, camphor, carbomer, DMDM hydantoin, edetate disodium, isoceteth-20, isopropyl alcohol, PEG-40 hydrogenated castor oil, sodium hydroxide, water

Questions?

call 866-326-1313 (toll-free)